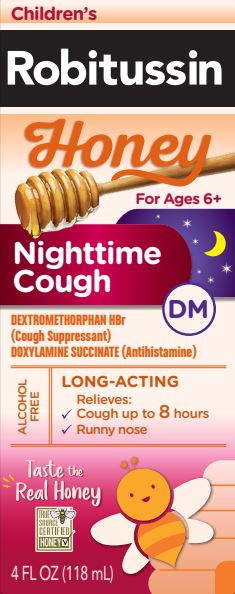 DRUG LABEL: Childrens Robitussin Honey Nighttime Cough DM
NDC: 0031-8762 | Form: SOLUTION
Manufacturer: Haleon US Holdings LLC
Category: otc | Type: HUMAN OTC DRUG LABEL
Date: 20250513

ACTIVE INGREDIENTS: DEXTROMETHORPHAN HYDROBROMIDE 15 mg/10 mL; DOXYLAMINE SUCCINATE 6.25 mg/10 mL
INACTIVE INGREDIENTS: ANHYDROUS CITRIC ACID; CARBOXYMETHYLCELLULOSE SODIUM, UNSPECIFIED; GLYCERIN; LACTIC ACID, UNSPECIFIED FORM; HONEY; POLYETHYLENE GLYCOL, UNSPECIFIED; PROPYLENE GLYCOL; WATER; SODIUM BENZOATE; SODIUM CITRATE, UNSPECIFIED FORM; SODIUM GLUCONATE; SUCRALOSE; XANTHAN GUM; ZINC GLUCONATE

Drug Facts

Active ingredients (in each 10mL)

Dextromethorphan HBr, USP 15 mg

Doxylamine Succinate, USP 6.25 mg

Purposes

Cough Suppressant

Antihistamine

Uses

- temporarily relieves cough due to minor throat and bronchial irritation as may occur with a cold
- temporarily relieves these symptoms due to hay fever or other upper respiratory allergies:
  - runny nose
  - sneezing
  - itchy, watery eyes
  - itching of the nose or throat
- controls the impulse to cough to help you sleep

Warnings

Do not use

- to sedate a child or to make a child sleepy
- if you are now taking a prescription monoamine oxidase inhibitor (MAOI) (certain drugs for depression, psychiatric, or emotional conditions, or Parkinson's disease), or for 2 weeks after stopping the MAOI drug. If you do not know if your prescription drug contains an MAOI, ask a doctor or pharmacist before taking this product.

Ask a doctor before use if you have

- trouble urinating due to an enlarged prostate gland
- glaucoma
- a cough that occurs with too much phlegm (mucus)
- a breathing problem or chronic cough that lasts or as occurs with smoking, asthma, chronic bronchitis or emphysema

Ask a doctor or pharmacist before use if you aretaking sedatives or tranquilizers

When using this product

- do not use more than directed
- marked drowsiness may occur
- avoid alcoholic drinks
- alcohol, sedatives, and tranquilizers may increase drowsiness
- be careful when driving a motor vehicle or operating machinery
- excitability may occur, especially in children

Stop use and ask a doctor ifcough lasts more than 7 days, comes back, or is accompanied by fever, rash, or persistent headache. These could be signs of a serious condition.

PREGNANCY OR BREAST FEEDING

If pregnant or breast-feeding,ask a health professional before use.

Keep out of reach of children.In case of overdose, get medical help or contact a Poison Control Center right away.

Directions

- measure only with dosing cup provided
- keep dosing cup with product
- mL = milliliter
- do not take more than 4 doses in any 24-hour period

age | dose
children under 6 years | do not use
children 6 to under 12 years | 10 mL every 6 hours
adults and children 12 years and older | 20 mL every 6 hours

Other information

- each 10 mL contains: sodium 10 mg
- store at 20–25°C (68–77°F)

Inactive ingredients

anhydrous citric acid, blueberry juice concentrate, carboxymethylcellulose sodium, glycerin, lactic acid, natural and artificial flavors, natural grade A honey, polyethylene glycol, propylene glycol, purified water, sodium benzoate, sodium citrate, sodium gluconate, sucralose, xanthan gum, zinc gluconate

Questions or comments?

call weekdays from 9 AM to 5 PM EST at 1-800-245-1040

Additional Information

Packaged with Tamper-Evident bottle cap. Do Not Use if breakable ring is separated or missing.

Dist. by: Haleon, Warren, NJ 07059

©2024 Haleon or licensor.

Trademarks owned or licensed by Haleon.

For most recent product information, visit www.robitussin.com

Pat. Info www.productpats.com

Made in Canada

PRINCIPAL DISPLAY PANEL

Children's
Robitussin
Honey
For Ages 6+

Nighttime
Cough
DM

DEXTROMETHORPHAN HBR
(COUGH SUPPRESSANT)
DOXYLAMINE SUCCINATE (ANTIHISTAMINE)

ALCOHOL
FREE

LONG-ACTING

- Relieves:

- Cough up to 8hours
- Runny nose

Taste the
Real Honey

TRUE
SOURCE
CERTIFIED
HONEY ✓

4 FL OZ (118 mL)